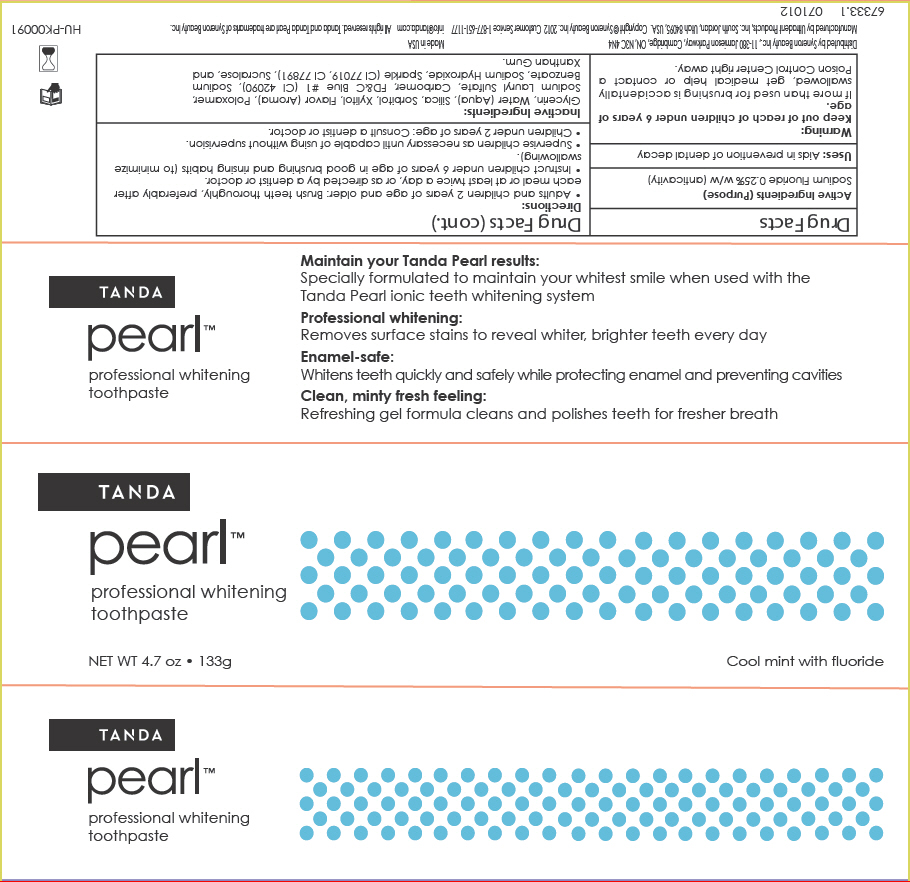 DRUG LABEL: Tanda pearl professional whitening
NDC: 46437-001 | Form: PASTE, DENTIFRICE
Manufacturer: Syneron Beauty Inc.
Category: otc | Type: HUMAN OTC DRUG LABEL
Date: 20120803

ACTIVE INGREDIENTS: Sodium Fluoride 0.33 g/133 g
INACTIVE INGREDIENTS: Glycerin; Water; Silicon Dioxide; Sorbitol; Xylitol; Methyl Salicylate; Sodium Lauryl Sulfate; FD&C Blue NO. 1; Sodium Benzoate; Sodium Hydroxide; Sucralose; Xanthan Gum

Tanda pearl™ professional whitening toothpaste

Drug Facts

Active Ingredients

Sodium Fluoride 0.25% w/w

Purpose

anticavity

Uses

Aids in prevention of dental decay

Warning

Keep out of reach of children under 6 years of age.

If more than used for brushing is accidentally swallowed, get medical help or contact a Poison Control Center right away.

Directions

- Adults and children 2 years of age and older: Brush teeth thoroughly, preferably after each meal or at least twice a day, or as directed by a dentist or doctor.
- Instruct children under 6 years of age in good brushing and rinsing habits (to minimize swallowing).
- Supervise children as necessary until capable of using without supervision.
- Children under 2 years of age: Consult a dentist or doctor.

Inactive Ingredients

Glycerin, Water (Aqua), Silica, Sorbitol, Xylitol, Flavor (Aroma), Poloxamer, Sodium Lauryl Sulfate, Carbomer, FD&C Blue #1 (CI 42090), Sodium Benzoate, Sodium Hydroxide, Sparkle (CI 77019, CI 77891), Sucralose, and Xanthan Gum.

Distributed by Syneron Beauty Inc., 11-380 Jamieson Parkway, Cambridge, ON, N3C 4N4

Manufactured by Ultradent Products, Inc. South Jordan, Utah 84095, USA.

PRINCIPAL DISPLAY PANEL - 133g Tube Carton

TANDA

pearl™

professional whitening
toothpaste

NET WT 4.7 oz • 133g

Cool mint with fluoride